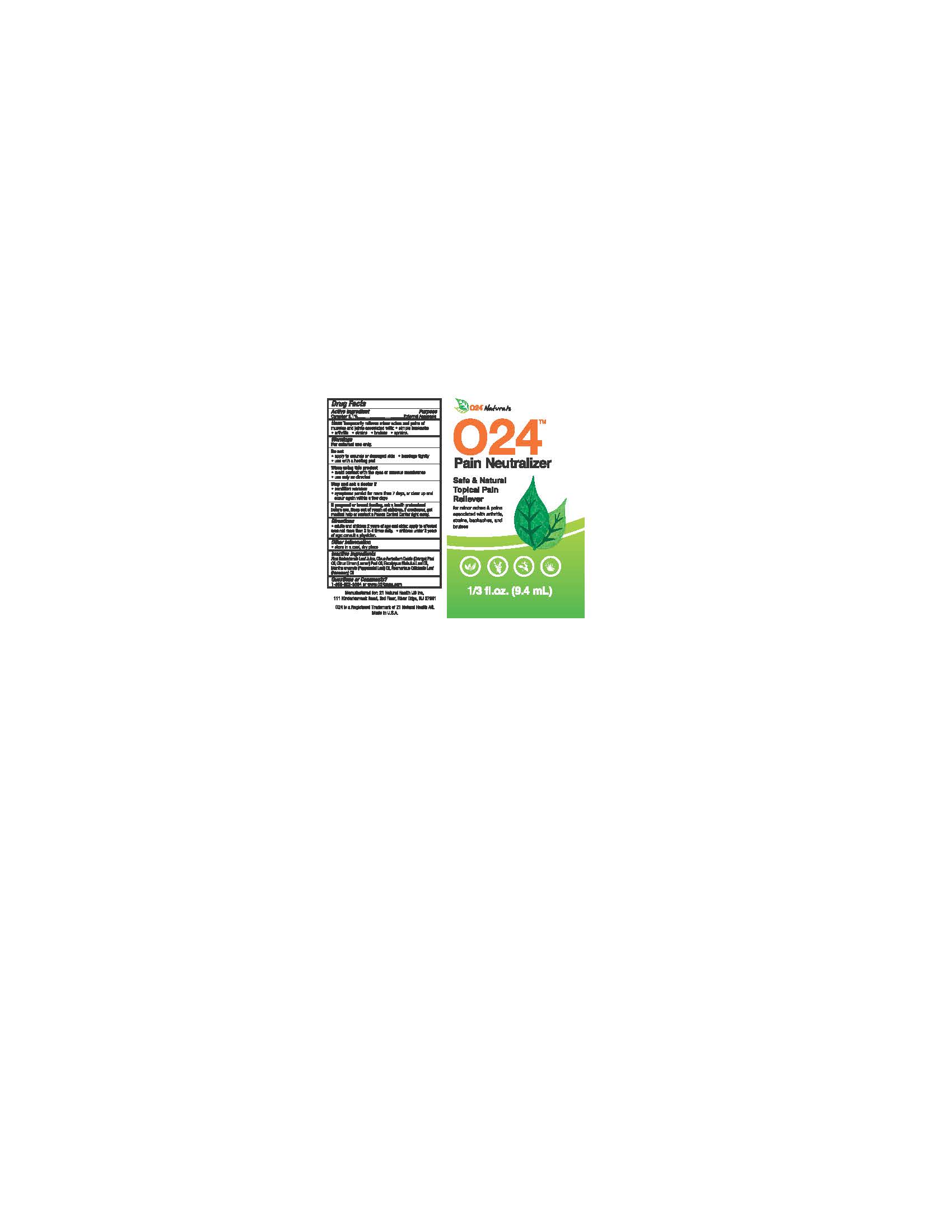 DRUG LABEL: O24 Pain Neutralizer
NDC: 72608-005 | Form: LIQUID
Manufacturer: D&d Essential Oils, Llc.,
Category: otc | Type: HUMAN OTC DRUG LABEL
Date: 20180211

ACTIVE INGREDIENTS: CAMPHOR (NATURAL) 3.1 g/100 mL
INACTIVE INGREDIENTS: ALOE VERA LEAF; ORANGE OIL; LEMON OIL; EUCALYPTUS OIL; LAVENDER OIL; MENTHA ARVENSIS LEAF OIL; ROSEMARY OIL

Drug Facts

Active Ingredient

Camphor 3.1%

Purpose

Camphor 3.1%..........................External Analgesic

Uses

Temporarily relieves minor aches and pains of muscles and joints associated with

- simple backache
- arthritis
- strains
- bruises
- sprains

Warnings

For external use only.

Do not

- apply to wounds or damaged skin
- bandage tightly
- use with a heating pad

When using this product

- avoid contact with the eyes or mucous membranes
- use only as directed.

Stop and ask a doctor if

- condition worsens
- symptoms persist for more than 7 days, or clear up and occur again within a few days

PREGNANCY OR BREAST FEEDING

If pregnant or breast feeding, ask a health professional before use.

Keep out of reach of children.

OTHER SAFETY INFORMATION

If swallowed, get medical help or contact a Poison Control Center right away.

Directions

- adults and children 2 years of age and older: apply to affected area not more than 3 to 4 times daily
- children under 2 years of age: consult a physician

Other Information

- store in a cool, dry place

Inactive Ingredients

Aloe Barbadensis Leaf Juice, Citrus Aurantium Dulcis (Orange) Peel Oil, Citrus Limon (Lemon) Peel Oil, Eucalyptus Globulus Leaf Oil, Lavandula Angustifolia (Lavender) Oil, Mentha arvensis (Peppermint Leaf) Oil, Rosmarinus Officinalis Leaf (Rosemary) Oil

Questions or Comments?

1-866-902-8594 or www.024zone.com

DESCRIPTION

Manufactured for

O24TM Naturals, LLC, 306 Hallmark Dr, Arlington, TX 76011

Questions?

Call TOLL-FREE: 1.866.902.8594 or visit us at: www.024zone.com

O24TM is a Registered Trademark of O24TM Naturals, LLC.

Made in U.S.A.

Active Ingredient
Camphor 3.1%

O24's Unique Process

Our unique process combines pure essential oils without the use of alcohol, glycerin, synthetics, chemical binding agents, or preservatives unlocking the full potential of all ingredients

Principal Display Panel

O24 Naturals

O24

Pain Neutralizer

Safe and Natural

Topical Pain Reliever

Rollover

for minor aches and pains associated with arthritis, strains, backaches, and bruises
1/3 fl.oz. (9.4 mL)